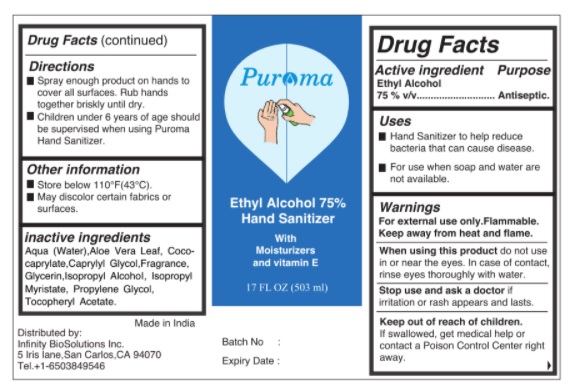 DRUG LABEL: PUROMA Hand sanitizer
NDC: 80948-003 | Form: LIQUID
Manufacturer: ZENITH MICRO CONTROL
Category: otc | Type: HUMAN OTC DRUG LABEL
Date: 20231213

ACTIVE INGREDIENTS: ALCOHOL 75 mL/100 mL
INACTIVE INGREDIENTS: WATER; ISOPROPYL ALCOHOL; GLYCERIN; ISOPROPYL MYRISTATE; .ALPHA.-TOCOPHEROL ACETATE; CAPRYLYL GLYCOL; ALOE VERA LEAF; PROPYLENE GLYCOL; COCO-CAPRYLATE; FRAGRANCE CLEAN ORC0600327

PUROMA Ethyl Alcohol 75% hand
Sanitizer

Active Ingredient

Alcohol 75% V/V

Purpose

Antiseptic.

Warnings

- Flammable. Keep away from fire or flame.
- When using this product do not use in or near theeyes. In case of contact, rinse eyes thoroughly with water.
- Stop use and ask a doctor if irritation or rash appears and lasts.

Uses

Hand Sanitizer to help reduce bacteria on skin.

Directions

- Spray enough product on hands to cover all surfaces. Rub hands together briskly until dry.

Keep out of reach of children.

If swallowed, get medical help or contact a poison control center right away.

Other information

- Store below 110°F (43°C).
- May discolor certain fabrics or surfaces.

Inactive Ingredients

WATER, ISOPROPYL ALCOHOL ,GLYCERIN, ISOPROPYL MYRISTATE,ALPHA.-TOCOPHEROL ACETATE, CAPRYLYL GLYCOL, ALOE VERA LEAF, PROPYLENE GLYCOL,COCO-CAPRYLATE , FRAGRANCE.